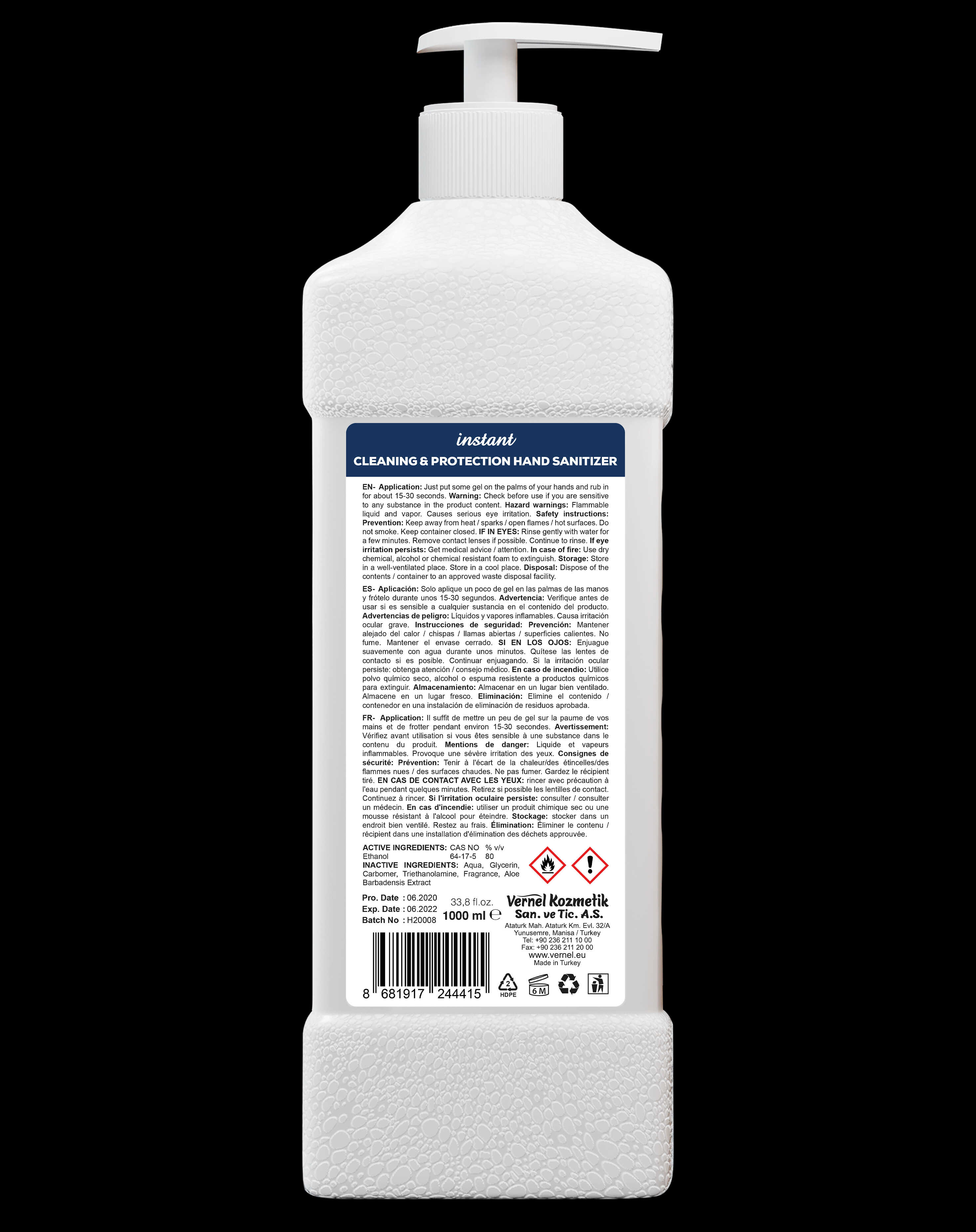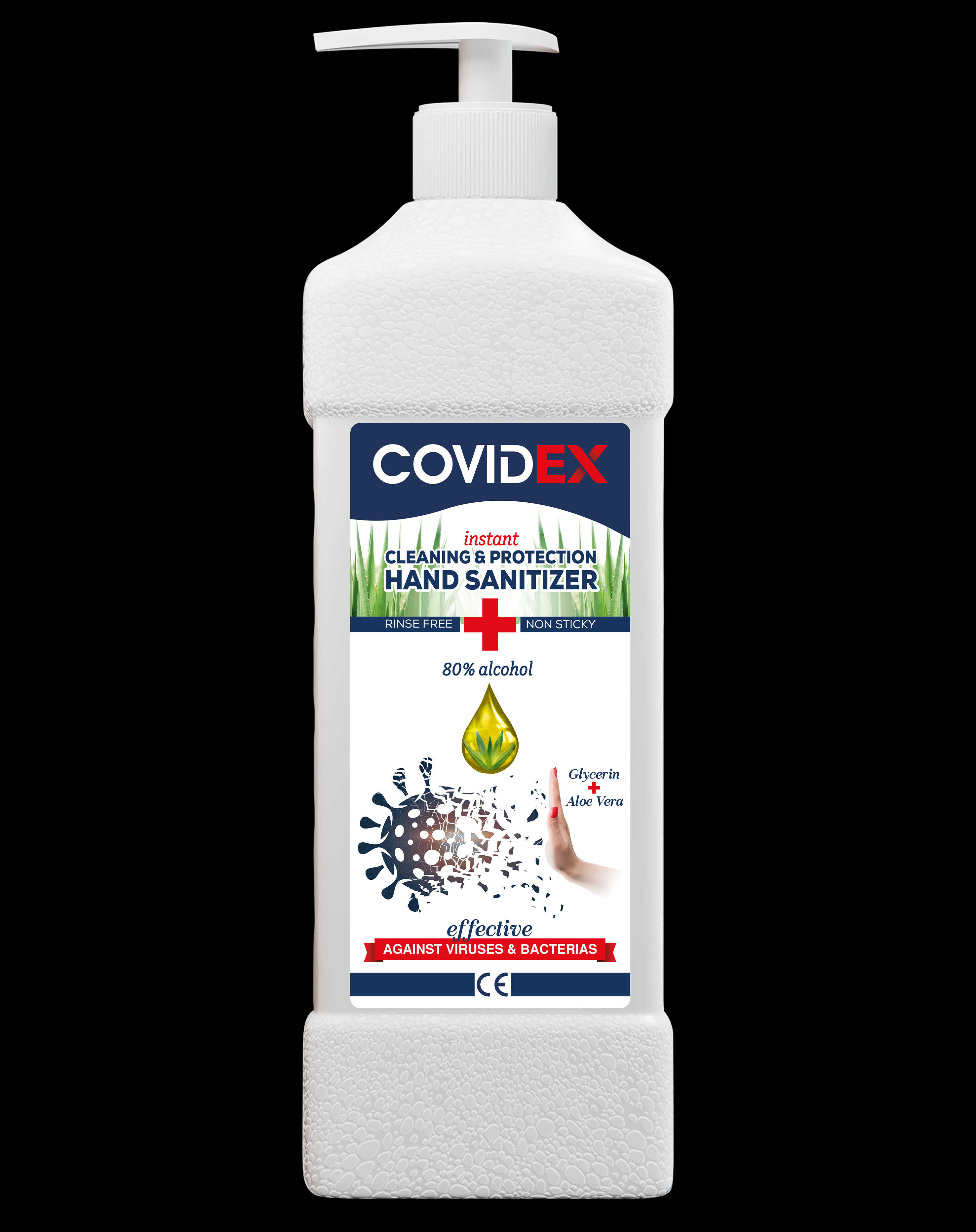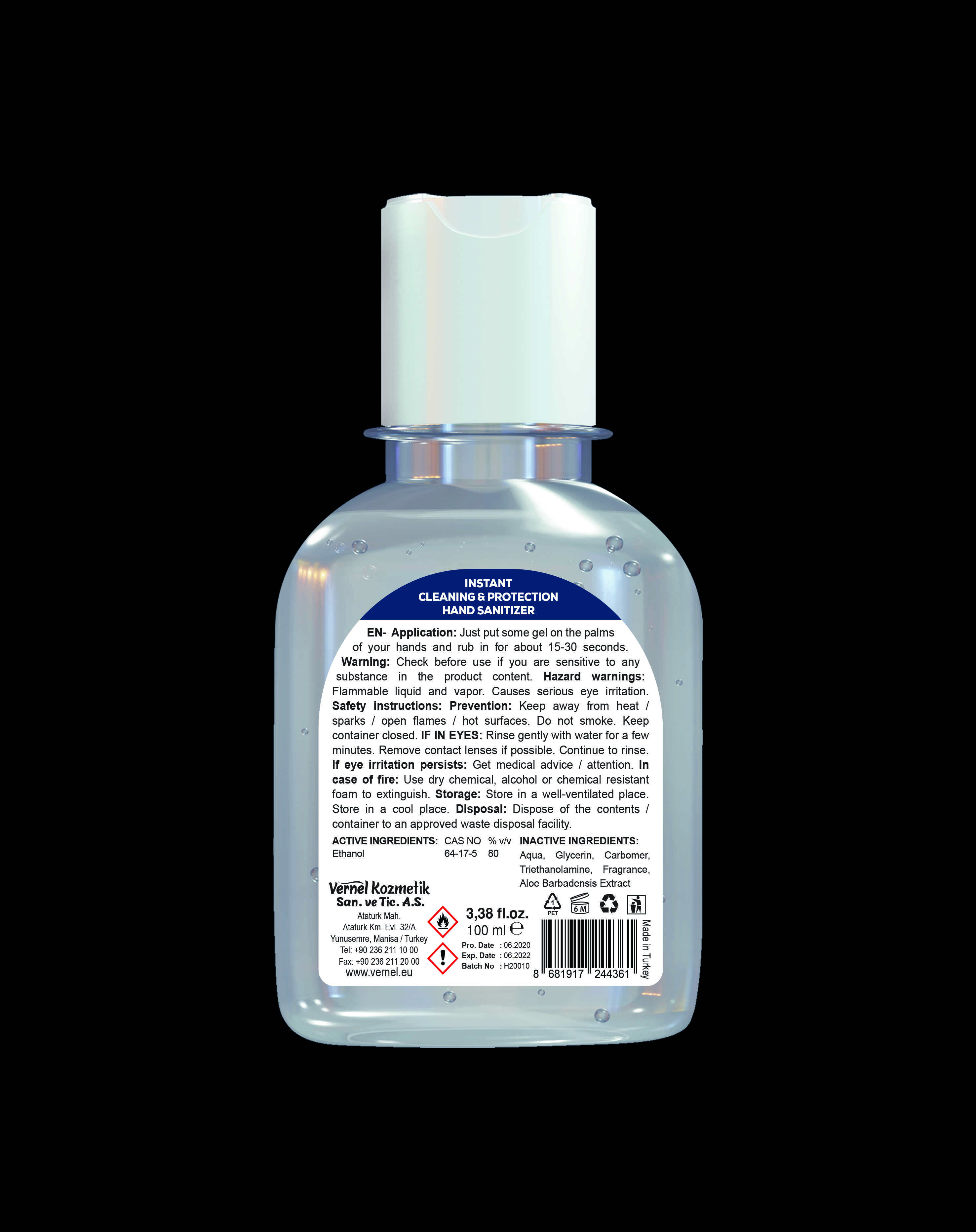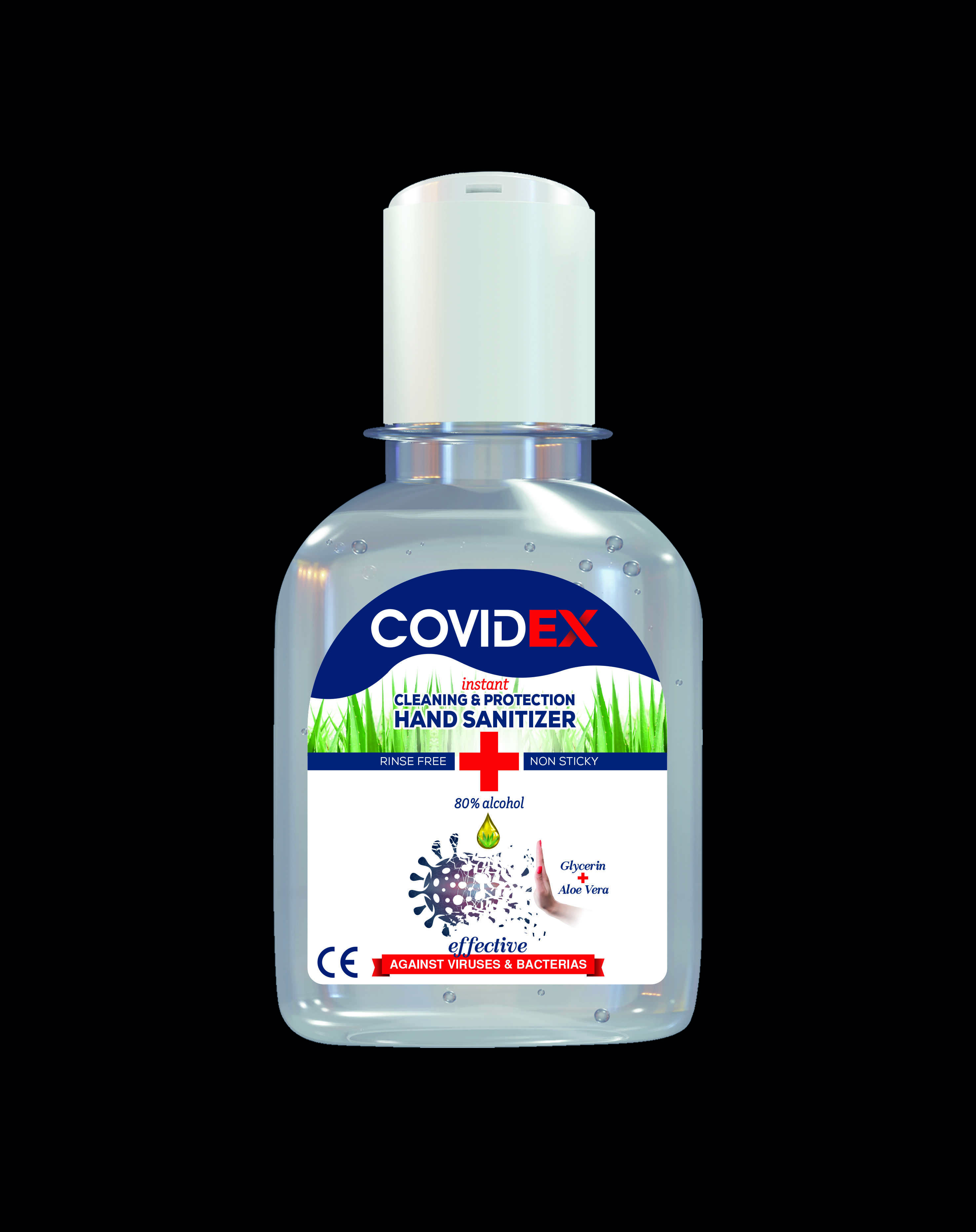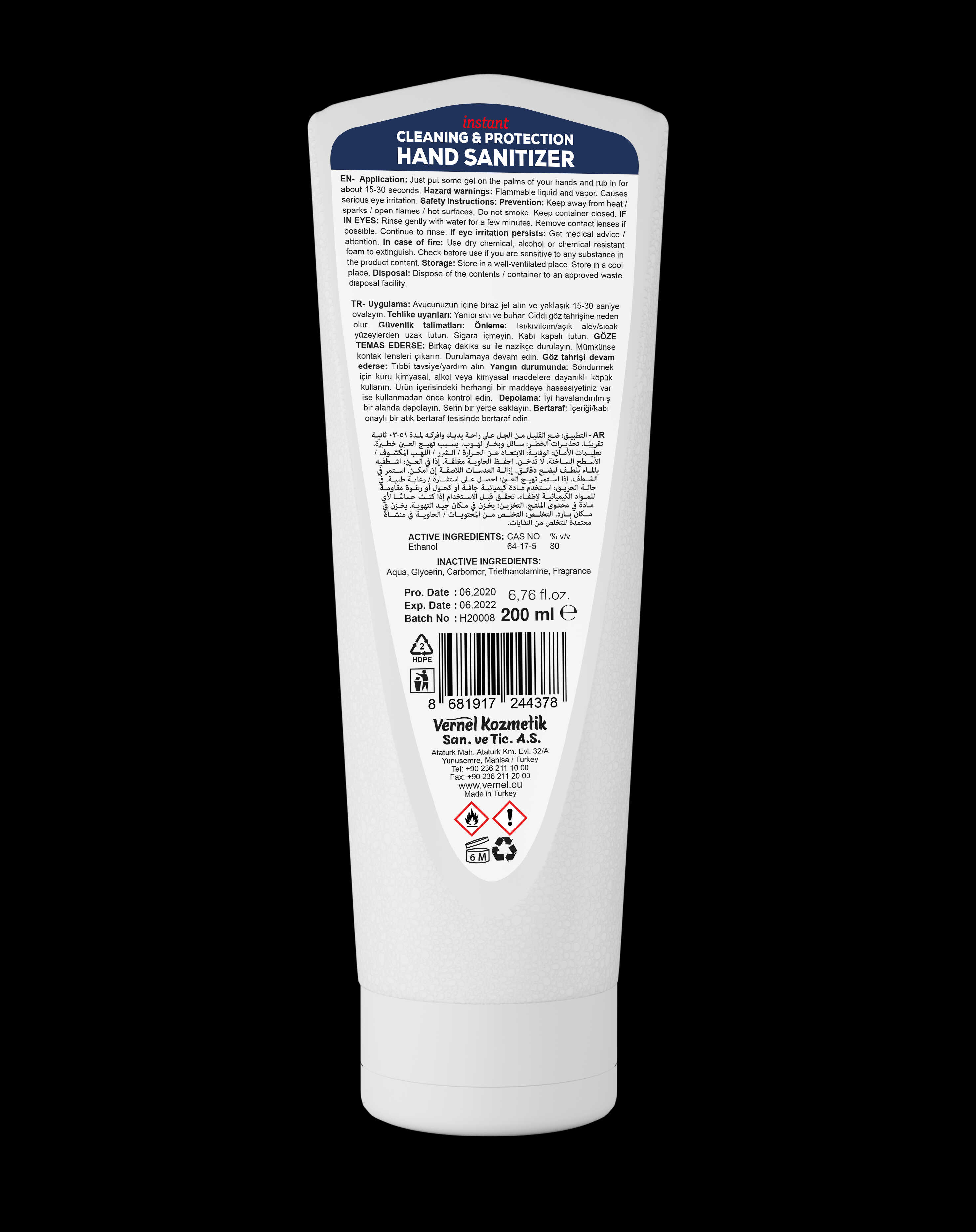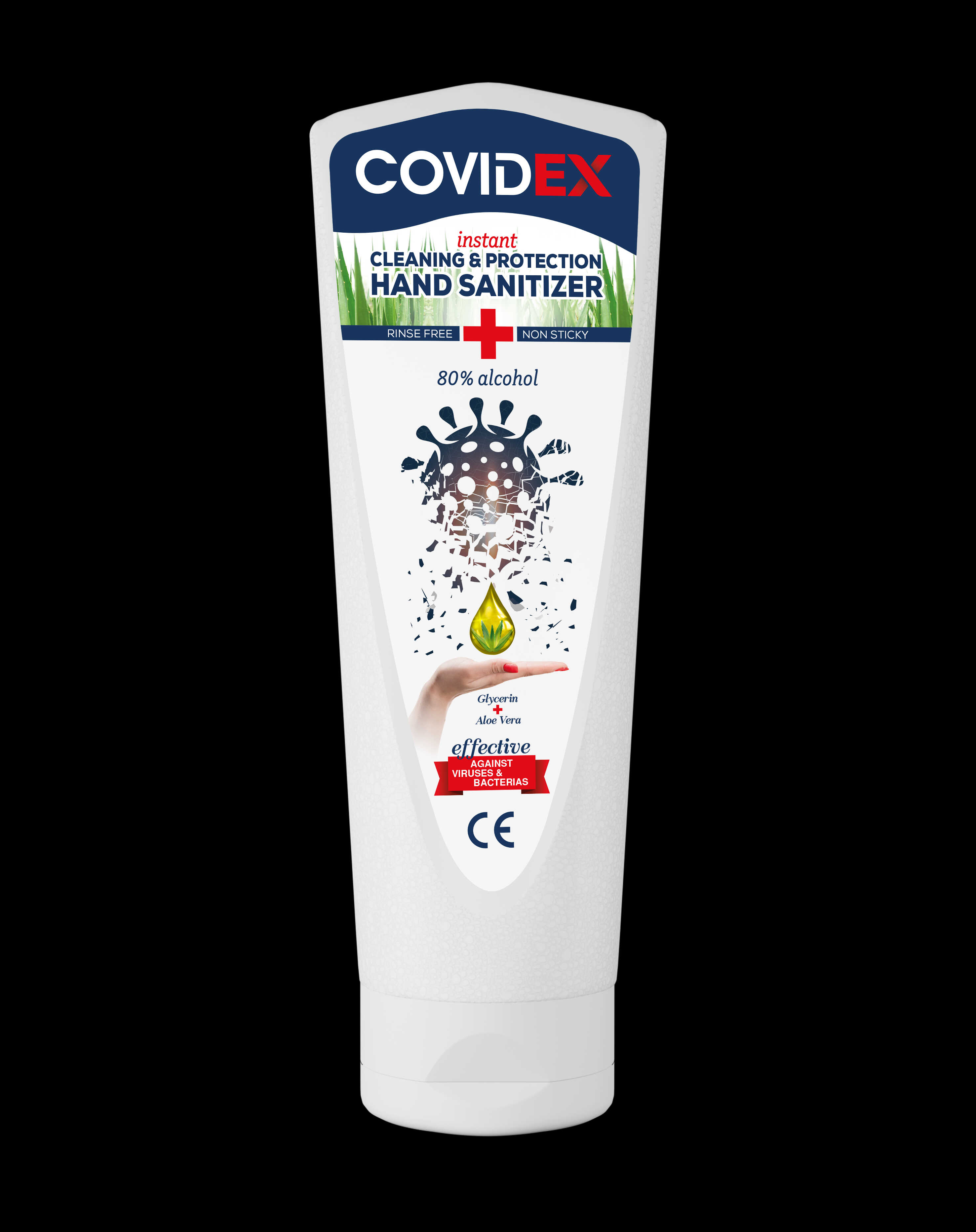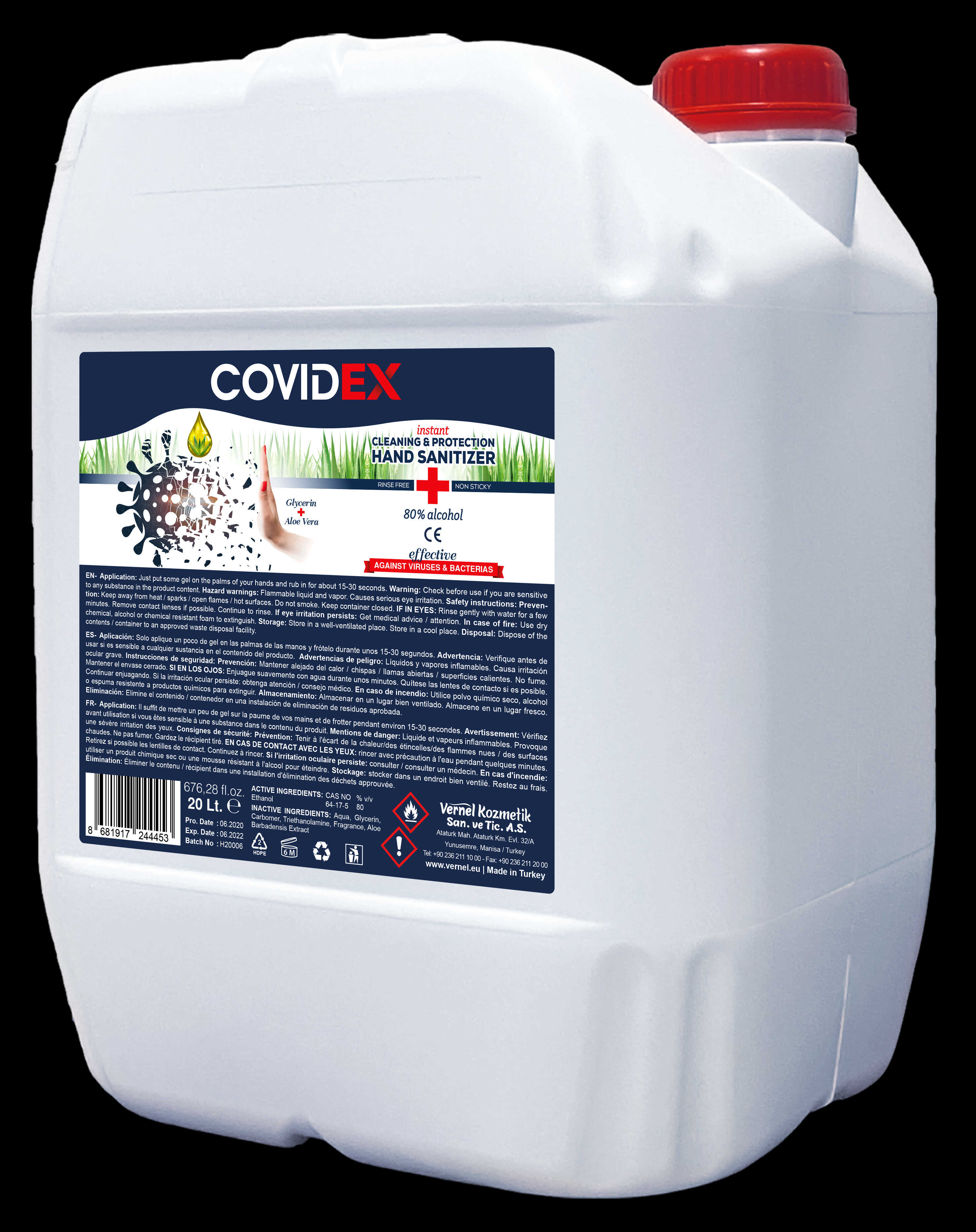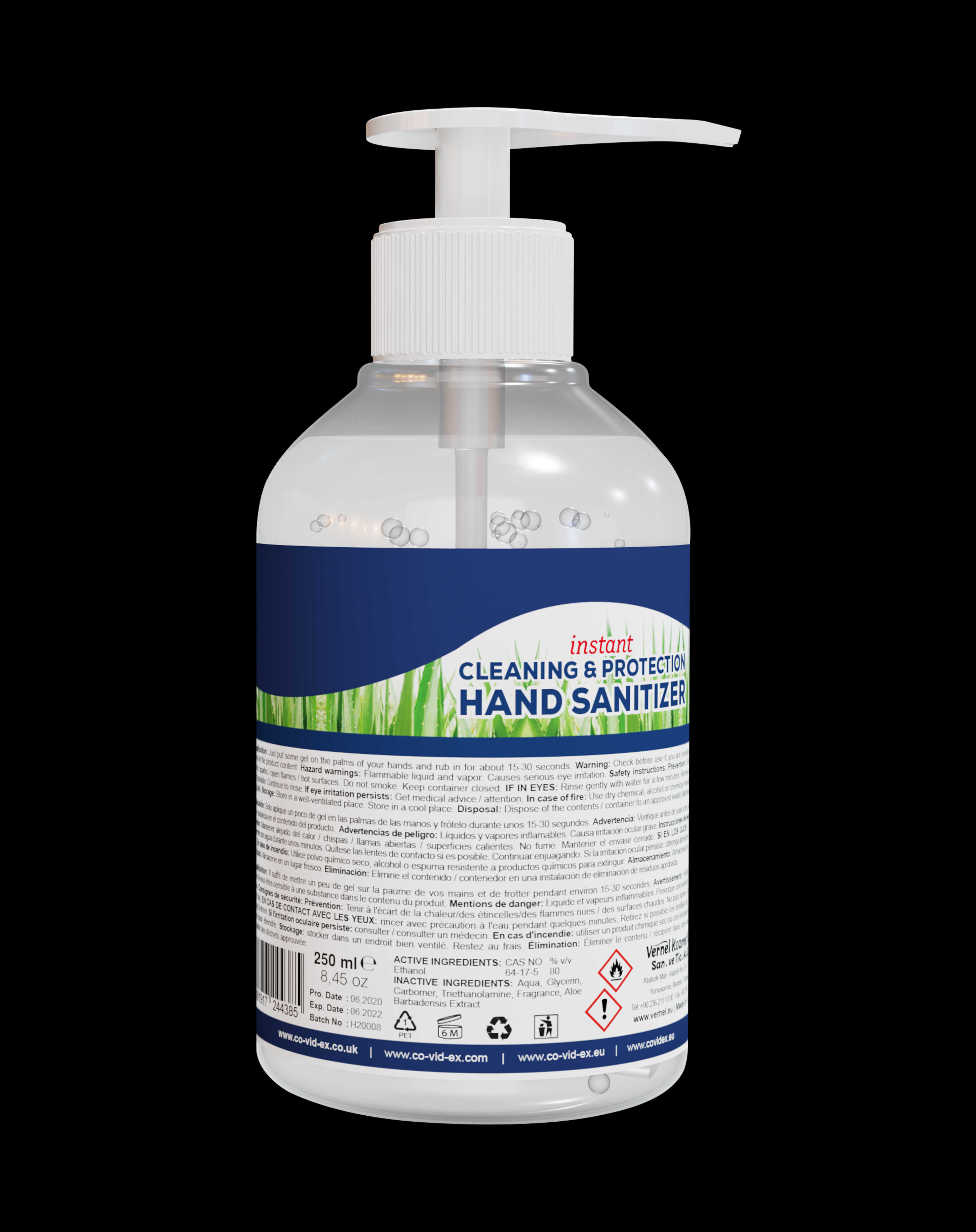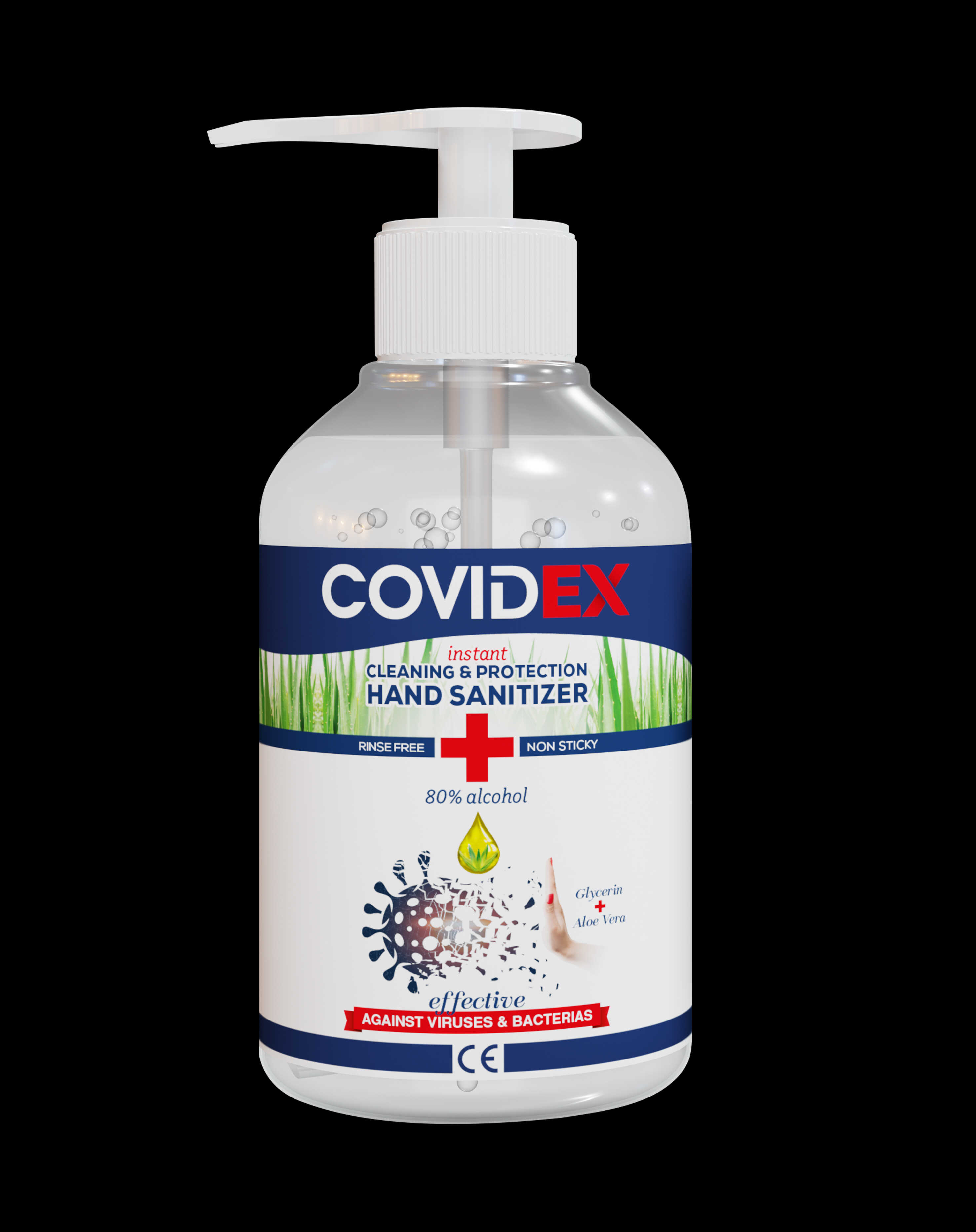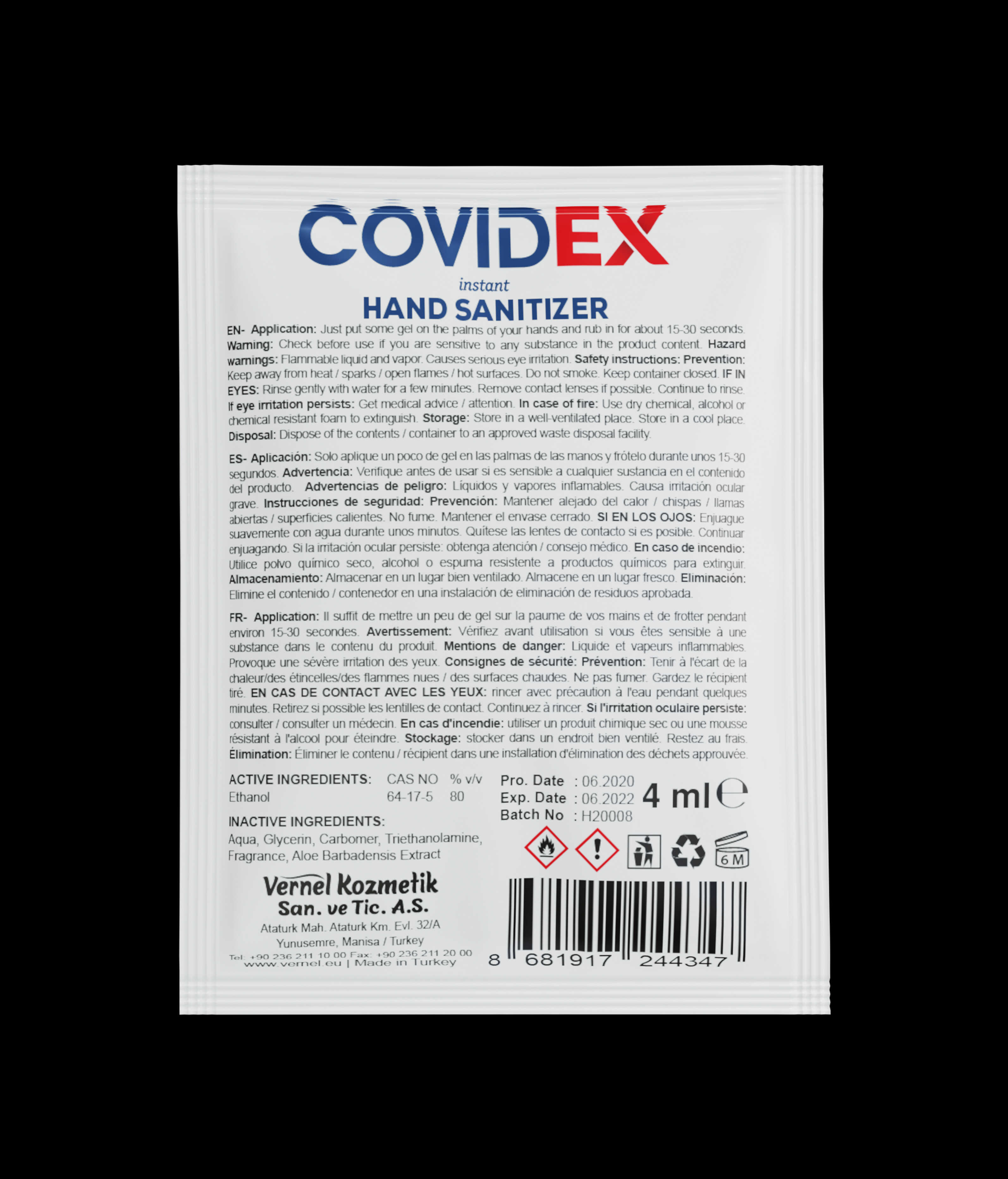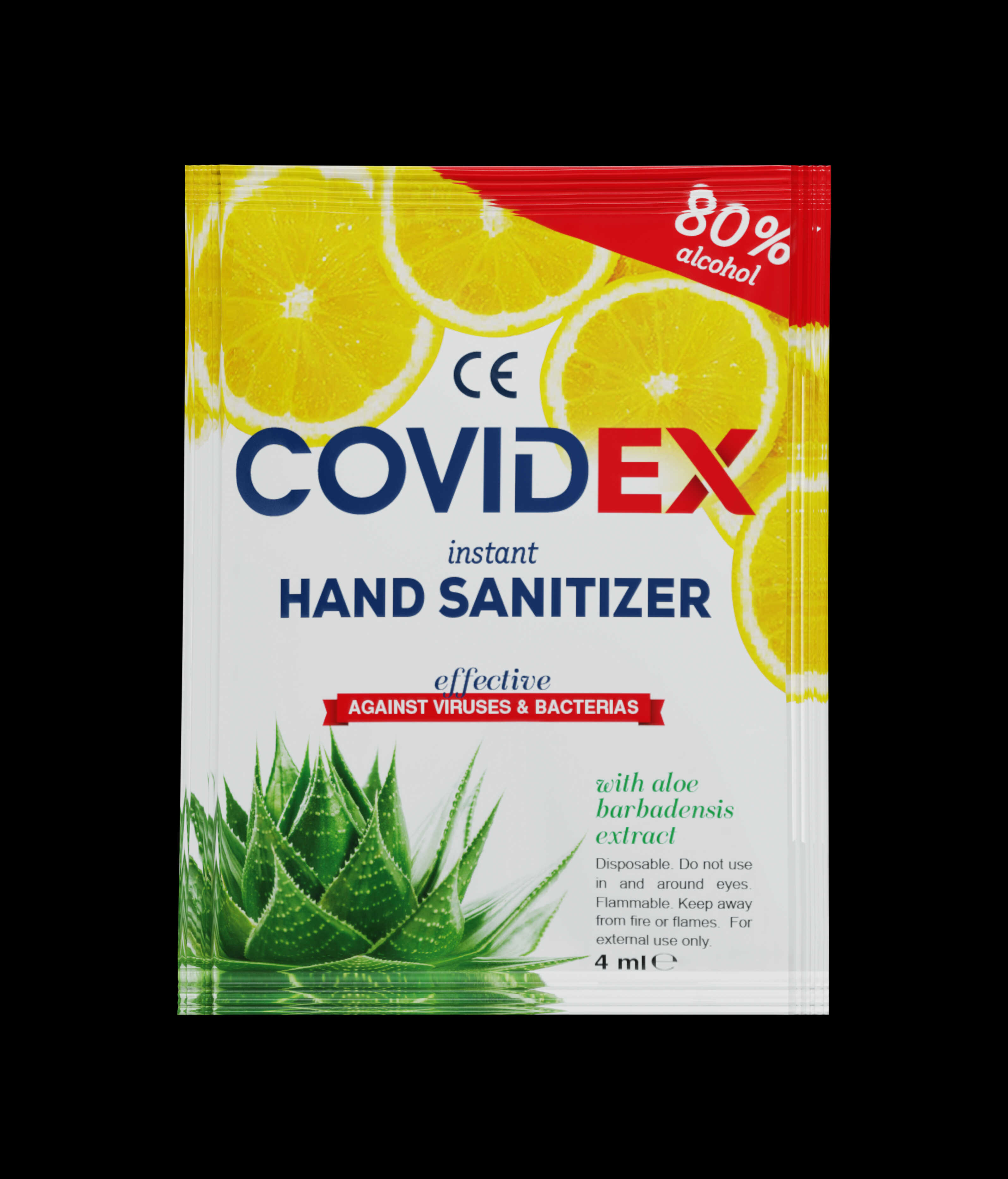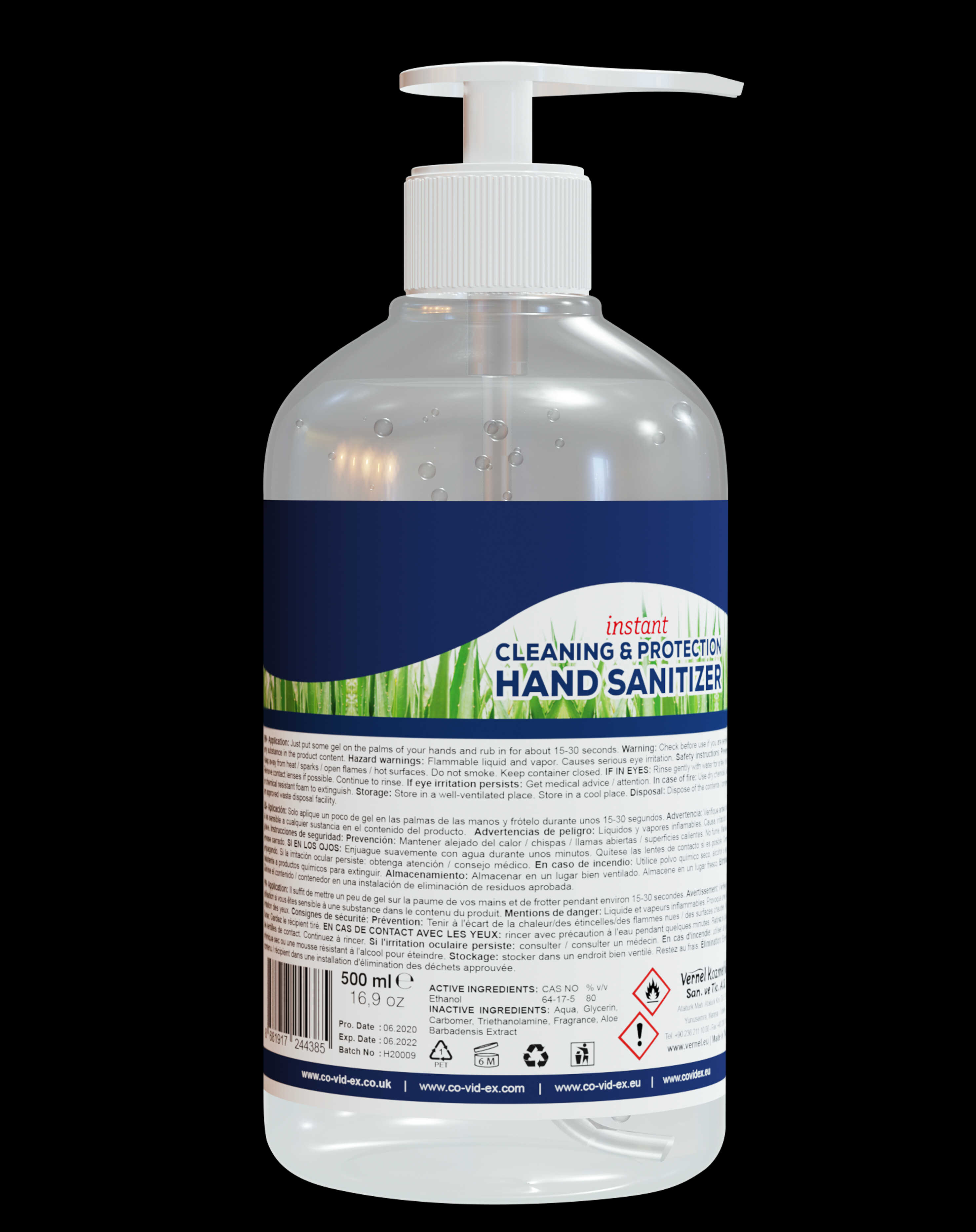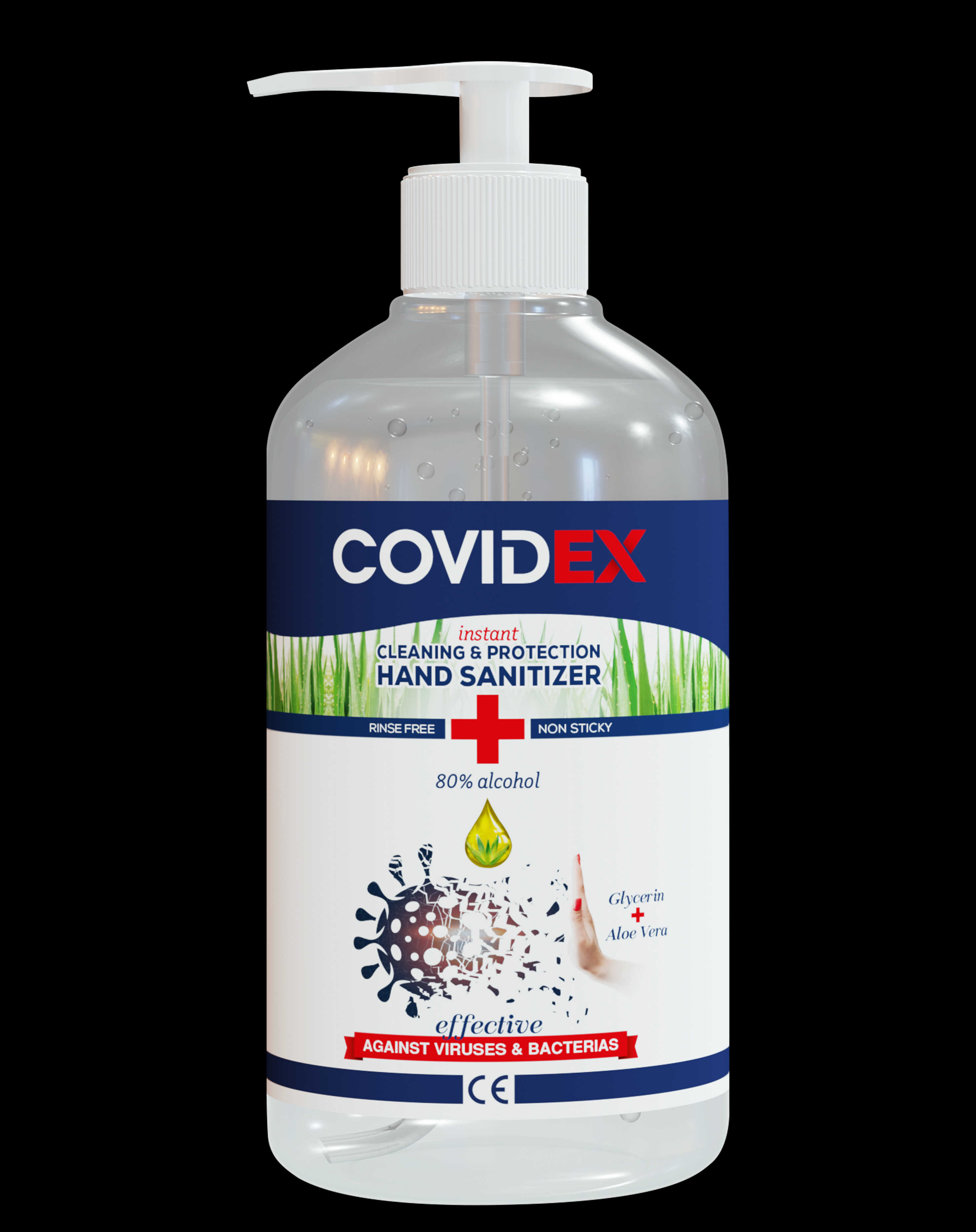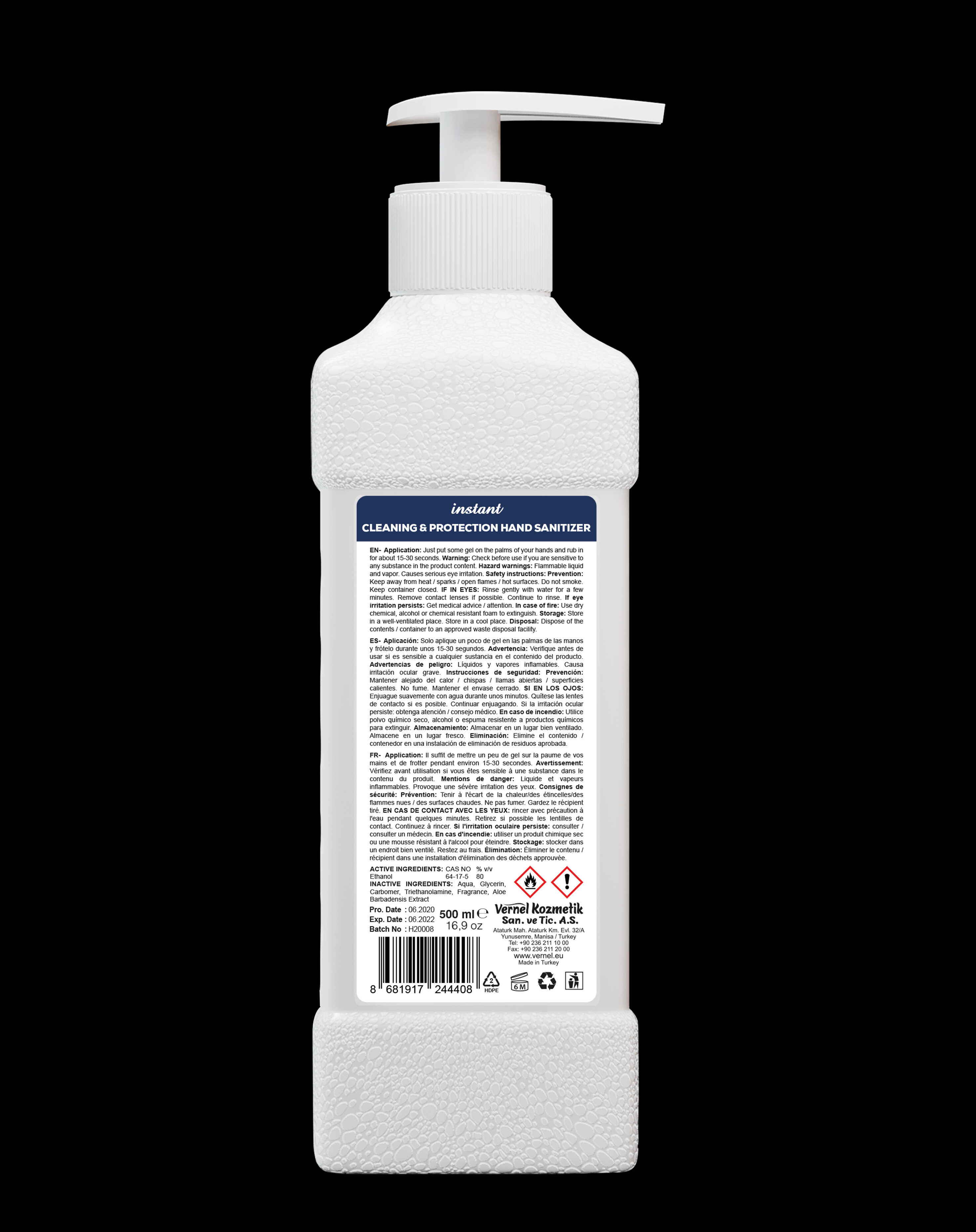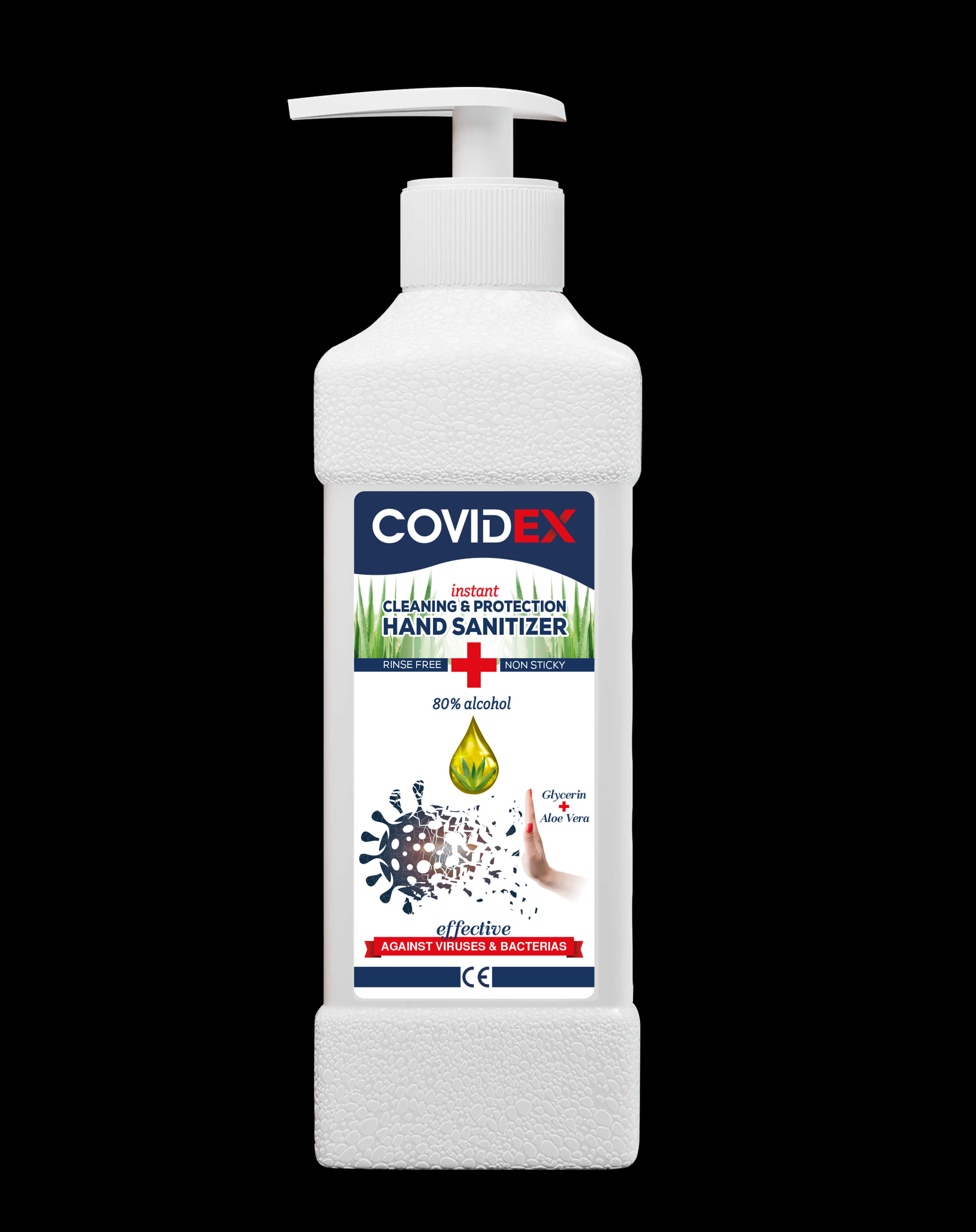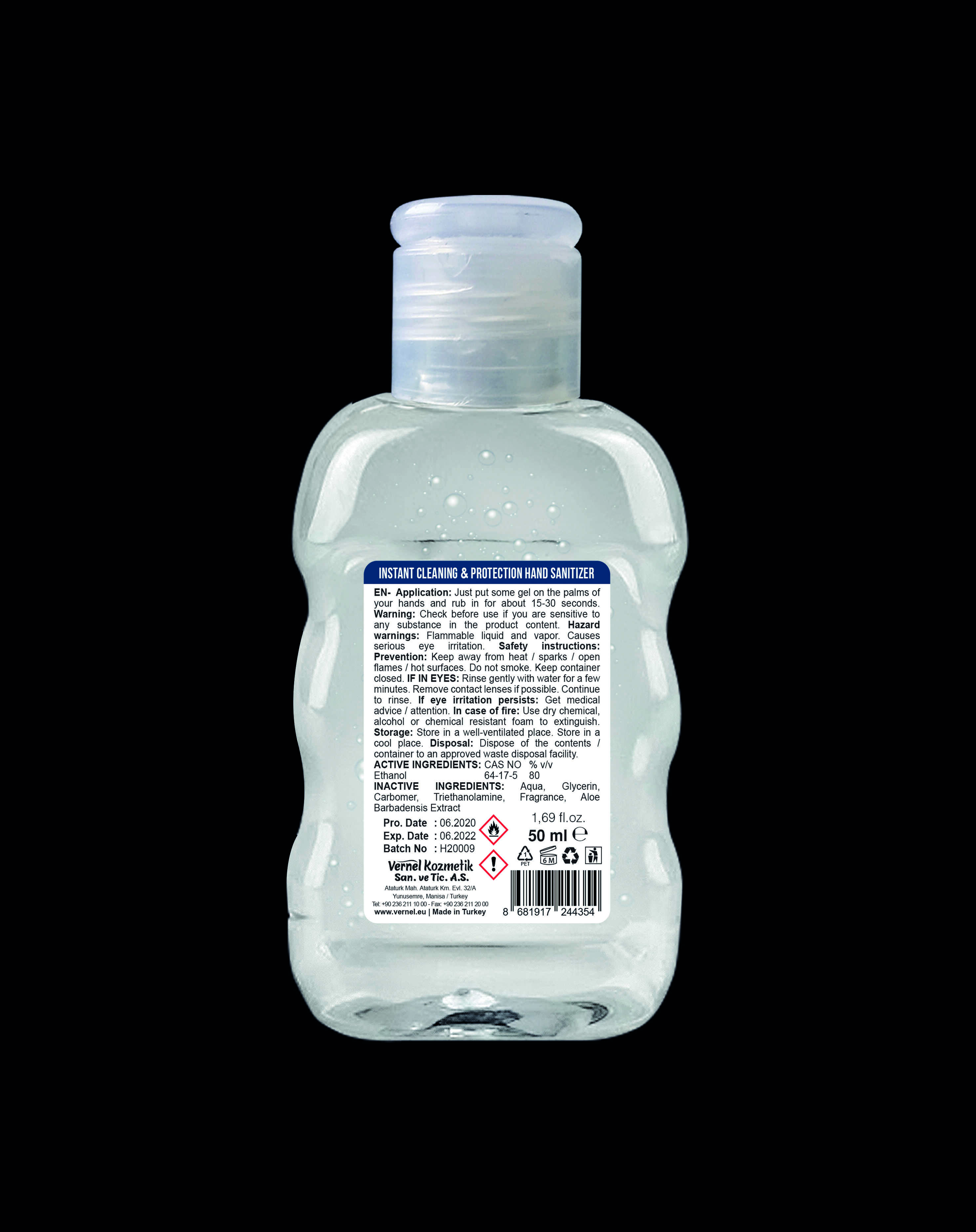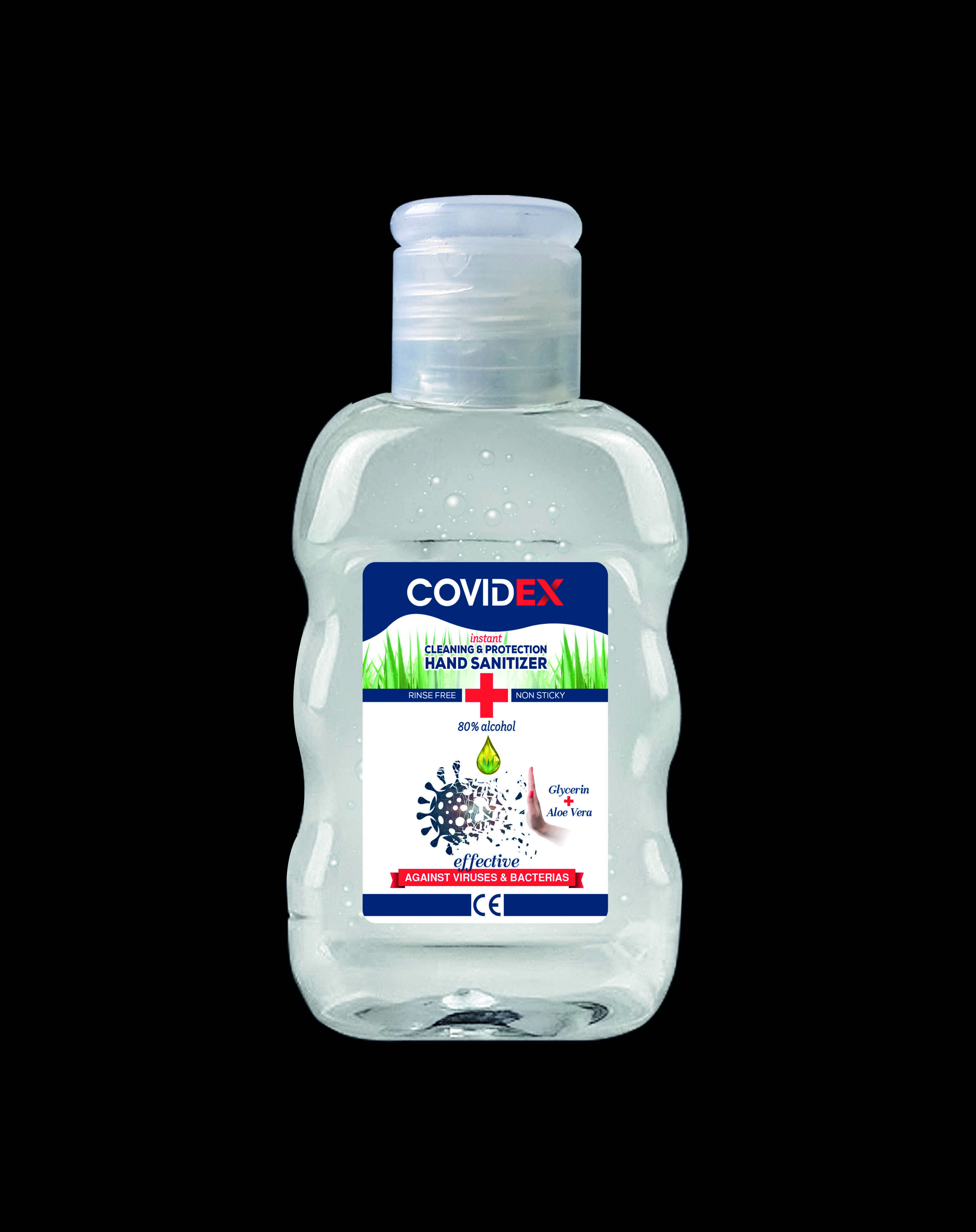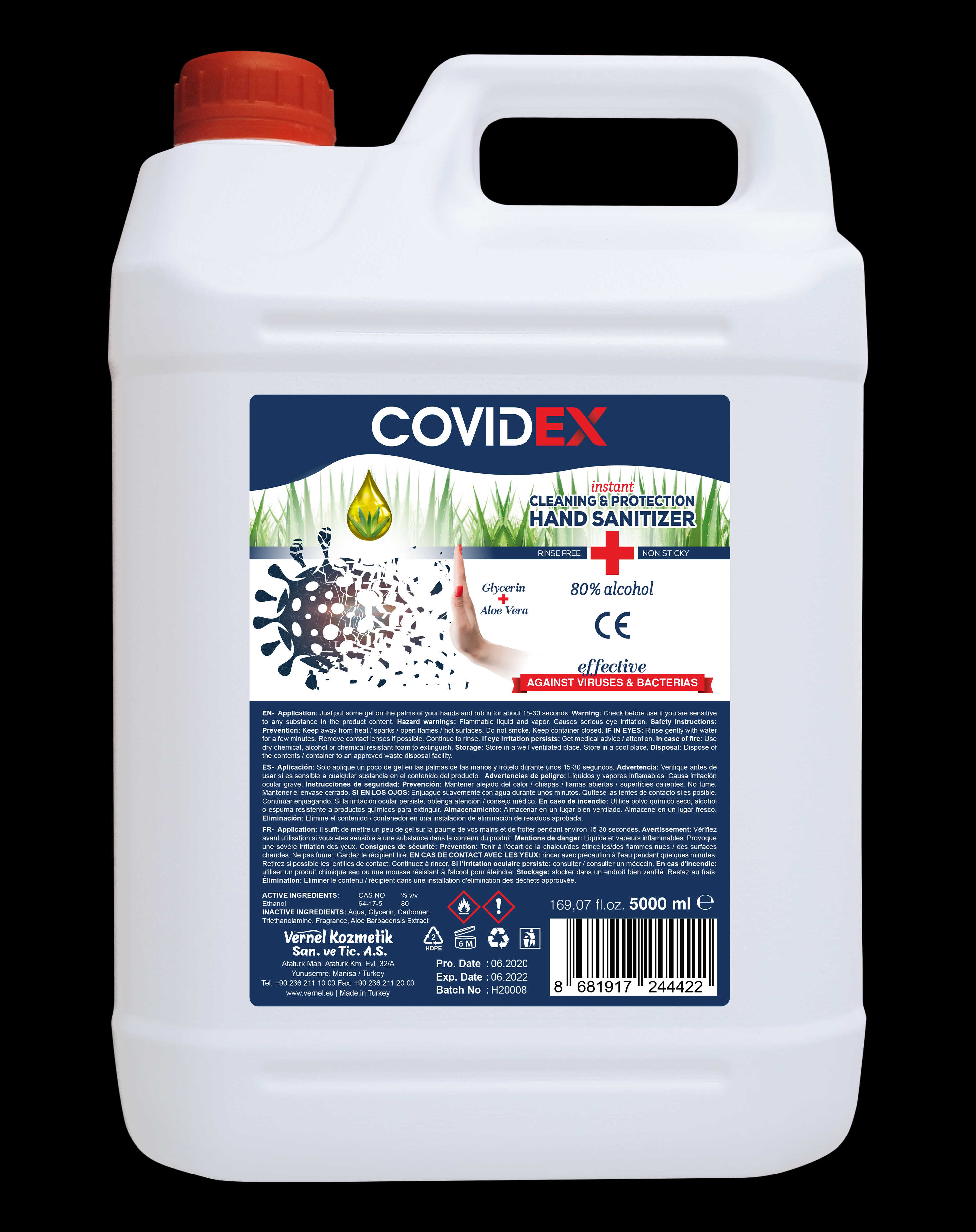 DRUG LABEL: COVIDEX
NDC: 79652-005 | Form: GEL
Manufacturer: VERNEL KOZMETIK SANAYI VE TICARET ANONIM SIRKETI
Category: otc | Type: HUMAN OTC DRUG LABEL
Date: 20200821

ACTIVE INGREDIENTS: ALCOHOL 75 mL/100 mL
INACTIVE INGREDIENTS: WATER 24.716 mL/100 mL; CARBOMER 940 0.47 mL/100 mL; GLYCERIN 1.18 mL/100 mL; TROLAMINE 0.24 mL/100 mL; ALOE VERA LEAF 0.12 mL/100 mL; FRAGRANCE LEMON ORC2001060 0.83 mL/100 mL

ACTIVE INGREDIENT

alocohol 75% (v/v)

PURPOSE

Antiseptic, Hand Sanitizer

INACTIVE INGREDIENT

purified water, carbomer, aloe vera leaf, fragrance lemon,trietanolamine (trolamine)

Keep out of reach of children. If swallowed, get medical help or contact a Poison Control Center right away.

This is a hand sanitizer manufactured according to the Temporary Policy for Preparation of Certain Alcohol-Based Hand Sanitizer Products During the Public Health Emergency (CoViD-19); Guidance for Industry.

The hand sanitizer is manufactured using only the following United States Pharmacopoeia (USP) grade ingredients in the preparation of the product

Alcohol (ethanol) (USP or Food Chemical Codex (FCC) grade) (80%, volume/volume (v/v)) in an aqueous solution denatured according to Alcohol and Tobacco Tax and Trade Bureau regulations in 27 CFR part 20.
Glycerol (1.45% v/v).
Sterile distilled water or boiled cold water.

The firm does not add other active or inactive ingredients. Different or additional ingredients may impact the quality and potency of the product.

INDICATIONS AND USAGE

Place enough product on hands to cover all surfaces. Rub hands together until dry.
Supervise children under 6 years of age when using this product to avoid swallowing.

WARNINGS

For external use only. Flammable. Keep away from heat or flame

DO NOT USE

in children less than 2 months of age
on open skin wounds

STORAGE AND HANDLING

Store between 15-30C (59-86F)
Avoid freezing and excessive heat above 40C (104F)

PACKAGE LABEL

ACTIVE INGREDIENT

alcohol 75 % (v/v)